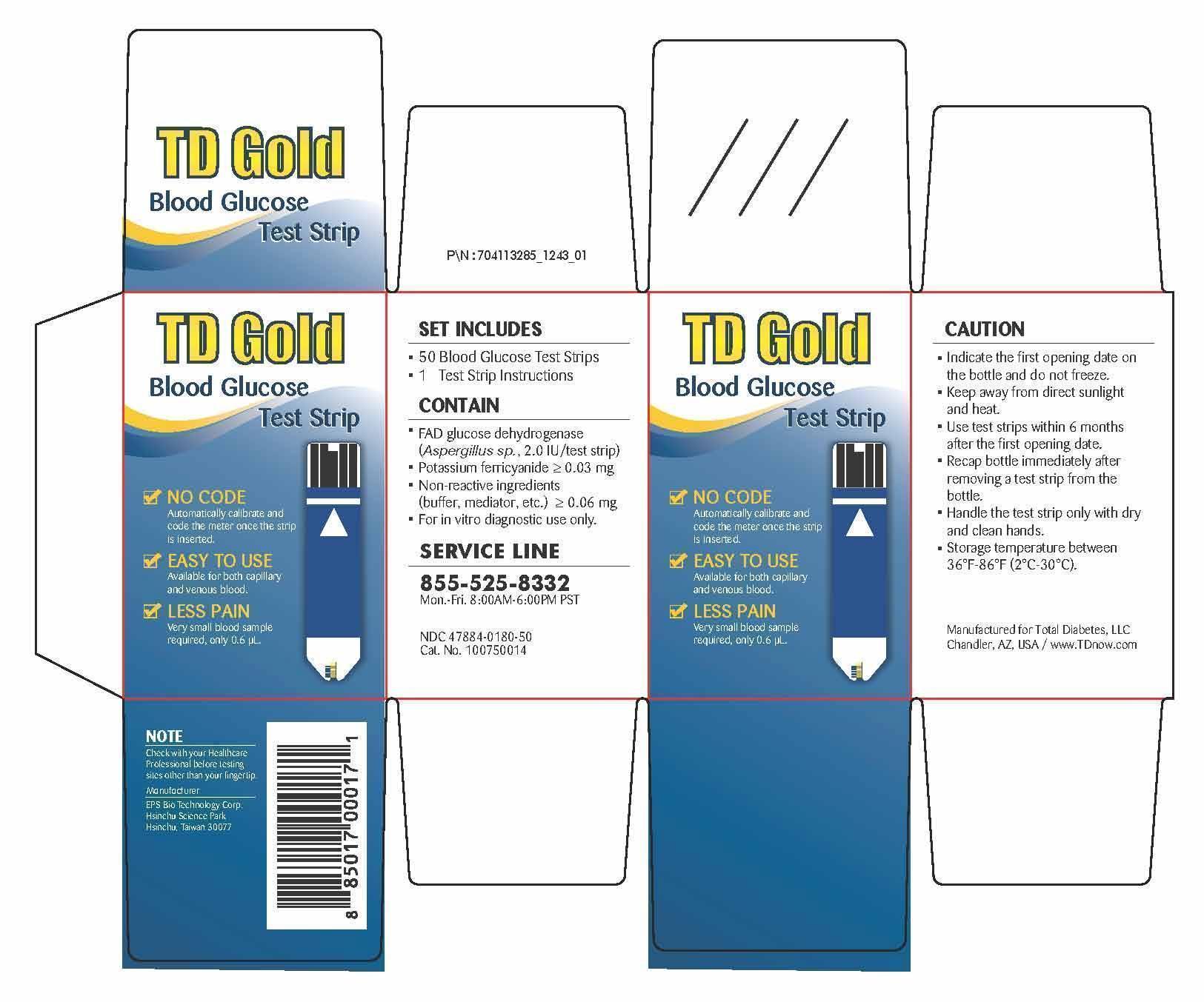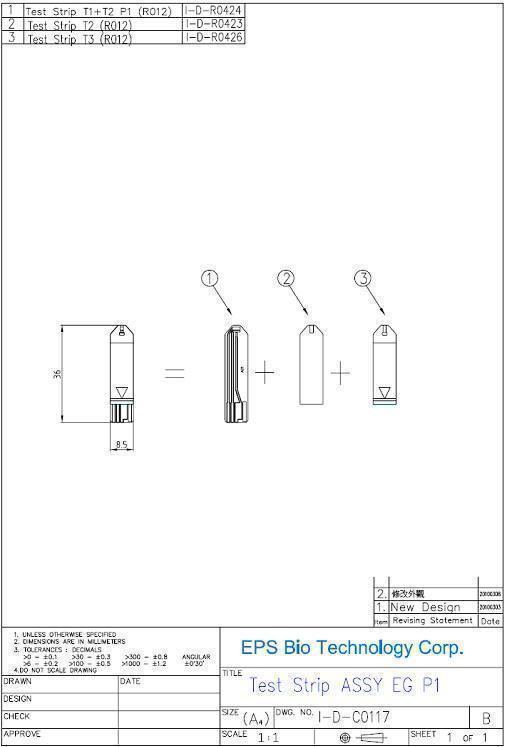 DRUG LABEL: TD Gold Blood Glucose Test Strip
NDC: 47884-180
Manufacturer: EPS Bio Technology Corp.
Category: other | Type: MEDICAL DEVICE
Date: 20130910

Home Use Medical Device:TD Gold Blood Glucose test strip